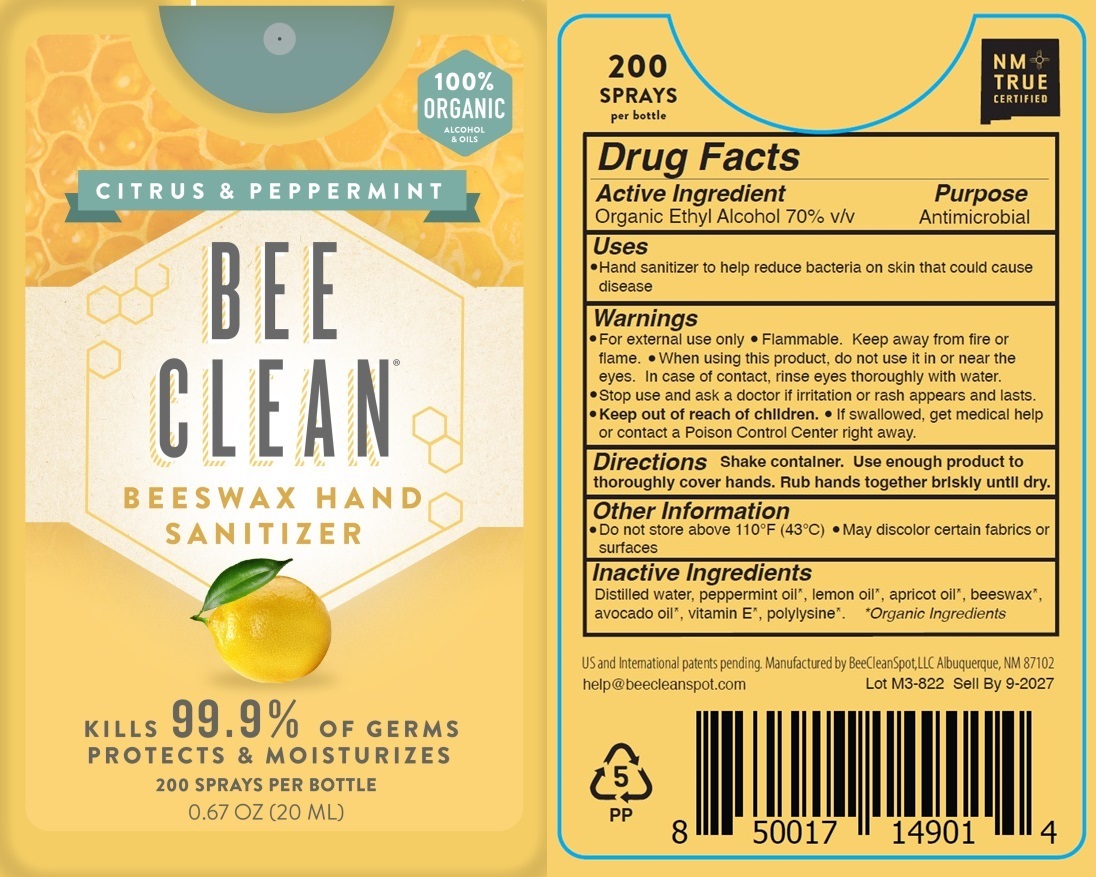 DRUG LABEL: Bee Clean - Beeswax Hand Sanitizer - Citrus and Peppermint
NDC: 81404-001 | Form: SPRAY
Manufacturer: BeeCleanSpot
Category: otc | Type: HUMAN OTC DRUG LABEL
Date: 20250929

ACTIVE INGREDIENTS: ALCOHOL 70 mL/100 mL
INACTIVE INGREDIENTS: WATER; .ALPHA.-TOCOPHEROL; POLY-L-LYSINE (30000-70000 MW); AVOCADO OIL; PEPPERMINT OIL; LEMON OIL; APRICOT KERNEL OIL; YELLOW WAX

Bee Clean - Beeswax Hand Sanitizer - Citrus and Peppermint

Active Ingredient

Organic Ethyl Alcohol 70% v/v

Purpose

Antimicrobial

Uses

- Hand sanitizer to help reduce bacteria on the skin that could cause disease

Warnings

- For external use only
- Flammable.
- Keep away from fire or flame.
- When using this product, do not use it on or in the eyes. In case of contact, rinse eyes thoroughly with water.

Stop use and ask a doctor if irritation or rash appears and lasts.

- Keep out of reach of children.
- If swallowed, get medical help or contact a Poison Control Center right away.

Directions

Shake container. Use enough product to thoroughly cover hands. Rub hands together briskly until dry.

Other Information

- Do not store above 110°F (43°C)
- May discolor certain fabrics or surfaces

Inactive Ingredients

Distilled water, peppermint oil*, lemon oil*, apricot oil*, beeswax*, avocado oil*, vitamin E*, polylysine*. * Organic Ingredients

PACKAGE LABEL

NDC: 81404-001-01

Bee Clean - Beeswax Hand Sanitizer - Citrus and Peppermint

200 Sprays Per Bottle

0.67 OZ (20 ML)